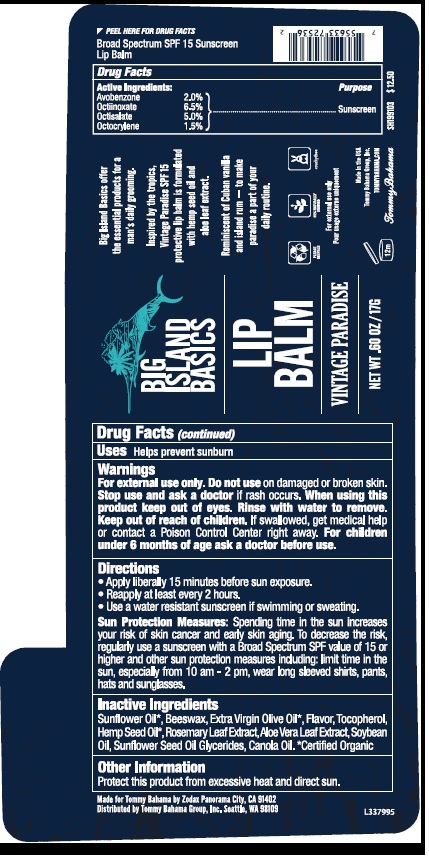 DRUG LABEL: Big Island Basics
NDC: 65692-1005 | Form: STICK
Manufacturer: Raining Rose, Inc.
Category: otc | Type: HUMAN OTC DRUG LABEL
Date: 20200410

ACTIVE INGREDIENTS: AVOBENZONE 20 mg/1 g; OCTINOXATE 65 mg/1 g; OCTISALATE 50 mg/1 g; OCTOCRYLENE 15 mg/1 g
INACTIVE INGREDIENTS: SUNFLOWER OIL; YELLOW WAX; OLIVE OIL; TOCOPHEROL; CANNABIS SATIVA SEED OIL; ROSEMARY; ALOE VERA LEAF; SOYBEAN OIL; SUNFLOWER OIL MONOGLYCERIDES; CANOLA OIL

Big Island Basics Lip Balm SPF 15 Sunscreen

Drug Facts

Active Ingredients
Avobenzone 2.0%
Octinoxate 6.5%
Octisalate 5.0%
Octocrylene 1.5%

Purpose

Avobenzone Sunscreen
Octinoxate Sunscreen
Octisalate Sunscreen
Octocrylene Sunscreen

INDICATIONS AND USAGE

Uses • Helps prevent sunburn

Warnings
For external use only • Do not use on damaged or broken skin.
Stop use and ask a doctor if rash occurs. When using this
product keep out of eyes. Rinse with water to remove.
Keep out of reach of children. If swallowed get medical help
or contact Poison Control Center right away. For children
under 6 months of age ask a doctor before use.

Directions

•Apply liberally 15 minutes before sun exposure
• Reapply at least every 2 hours
• Use a water resistant sunscreen if swimming or sweating

Sun Protection Measures. Spending time in the sun increases
your risk of skin cancer and early skin aging. To decrease this risk,
regularly use a sunscreen with a Broad-Spectrum SPF value of 15 or
higher and other sun protection measures including: limit time in the
sun, especially from 10 a.m. - 2 p.m. wear long-sleeved shirts, pants,
hats, and sunglasses

Inactive Ingredients
Sunflower Oil*, Beeswax, Extra Virgin Olive Oil*, Flavor, Tocopherol,
Hemp Seed Oil*, Rosemary Leaf Extract, Aloe Vera Leaf Extract, Soybean
Oil, Sunflower Seed Oil Glycerides, Canola Oil, *Certified Organic

Other Information: Protect this product from excessive
heat and sun.

Principal Display Package

BIG
ISLAND
BASICS

LIP
BALM

VINTAGE PARADISE

NET WT .60 OZ/17G

For external use only

Broad Spectrum SPF 15 Sunscreen
Lip Balm

Made for Zodax, Panorama City, CA 91402

Distributed by Tommy Bahana Group, Inc. Seattle, WA 98109

L341677

res